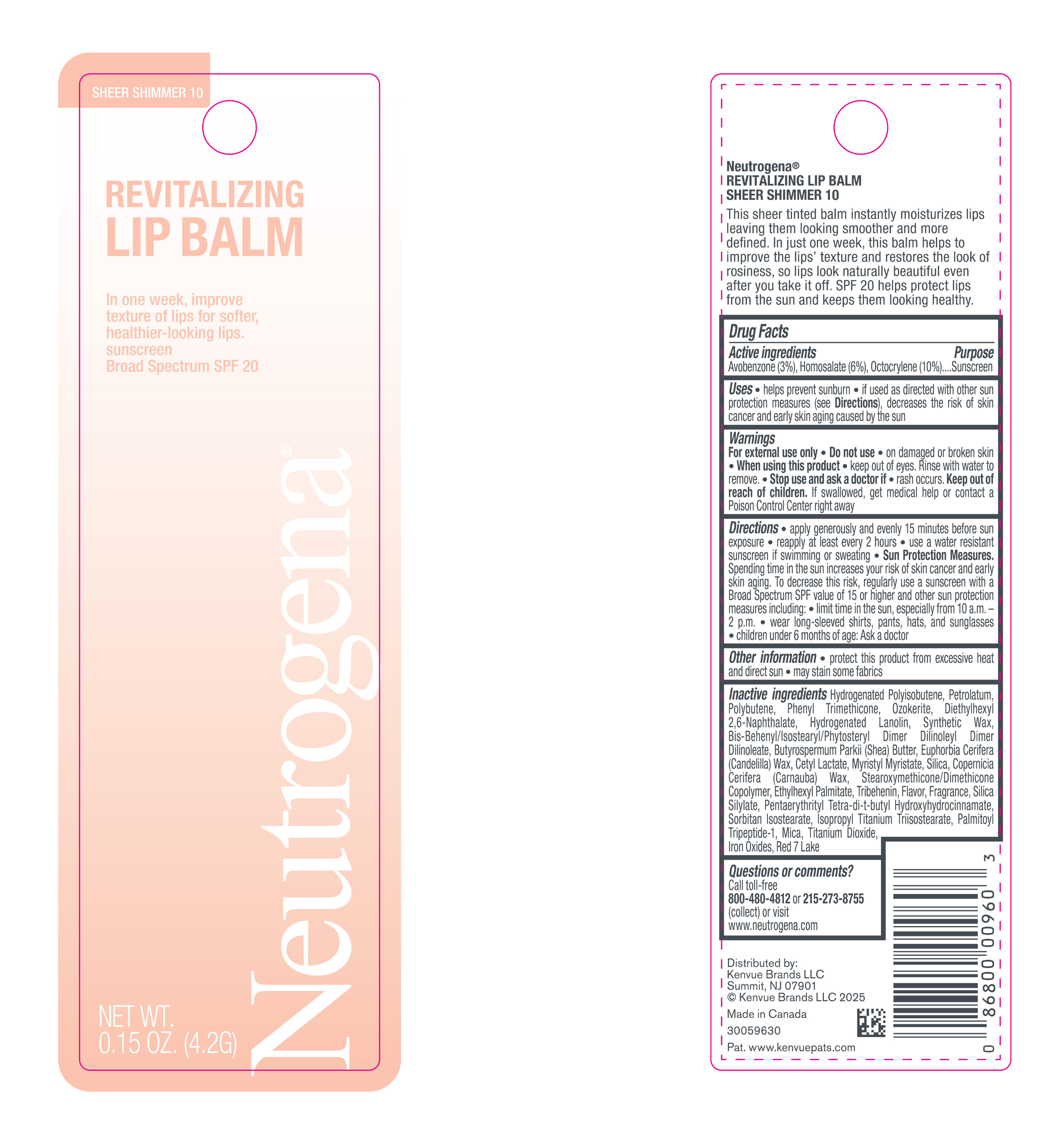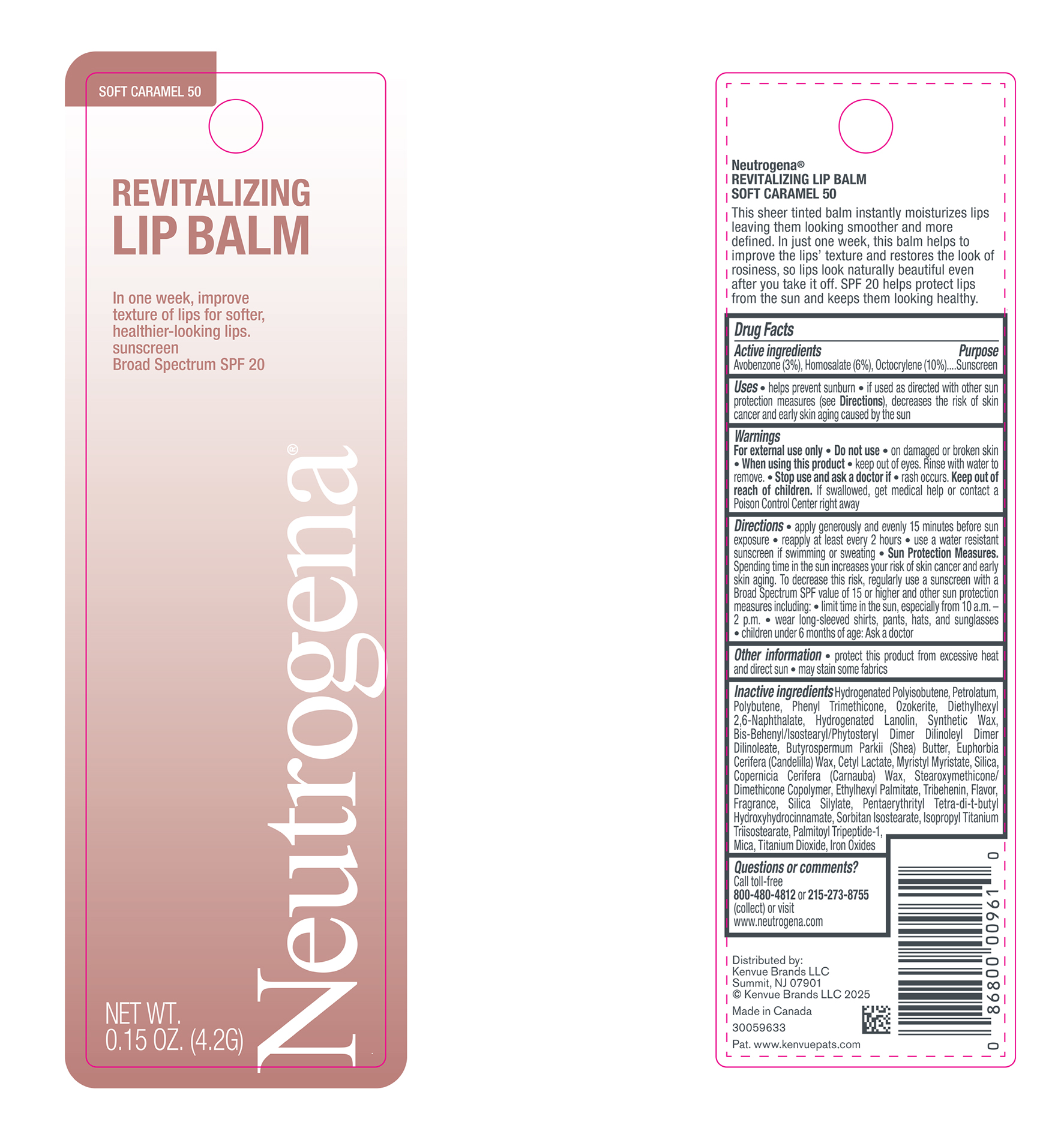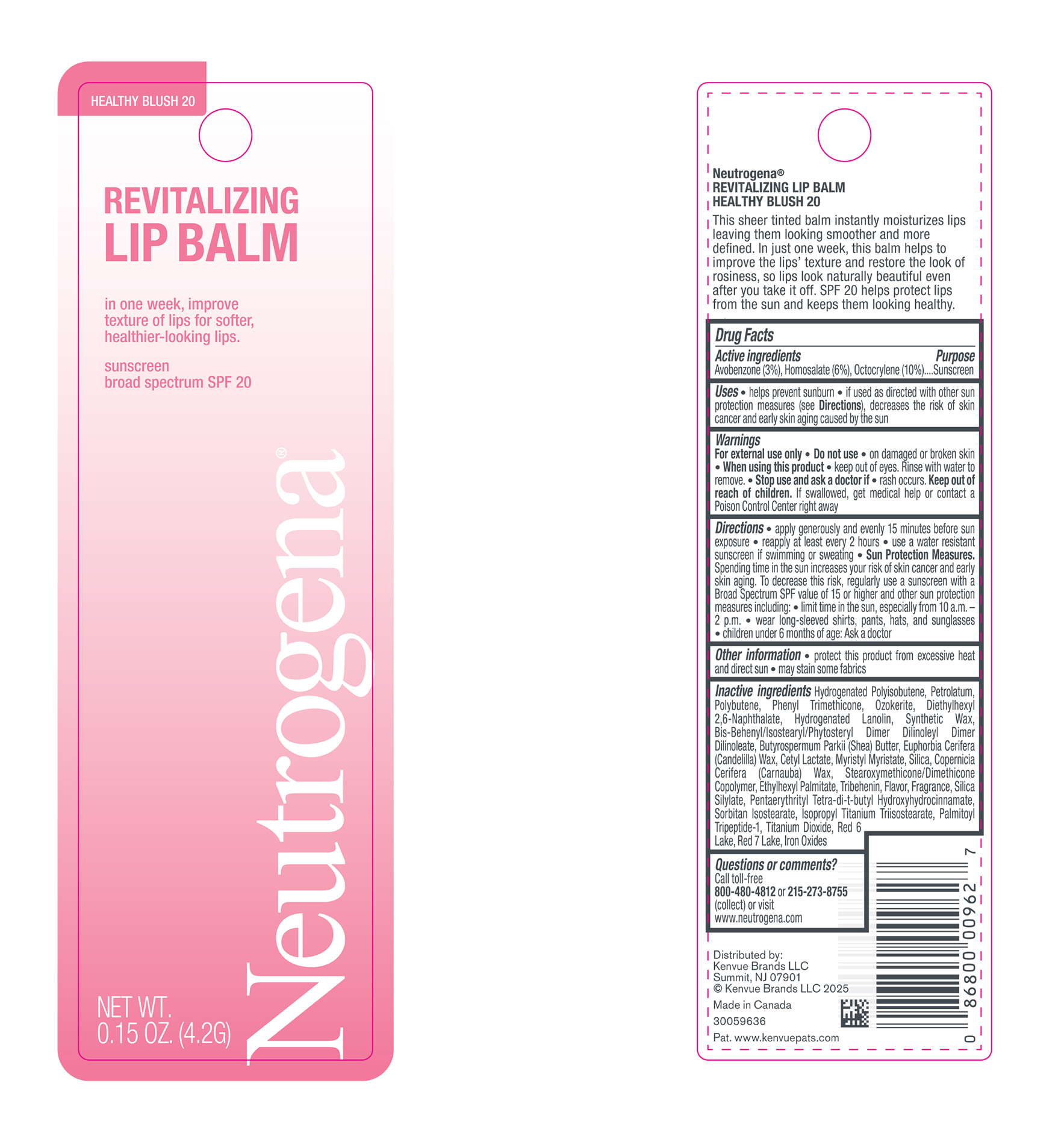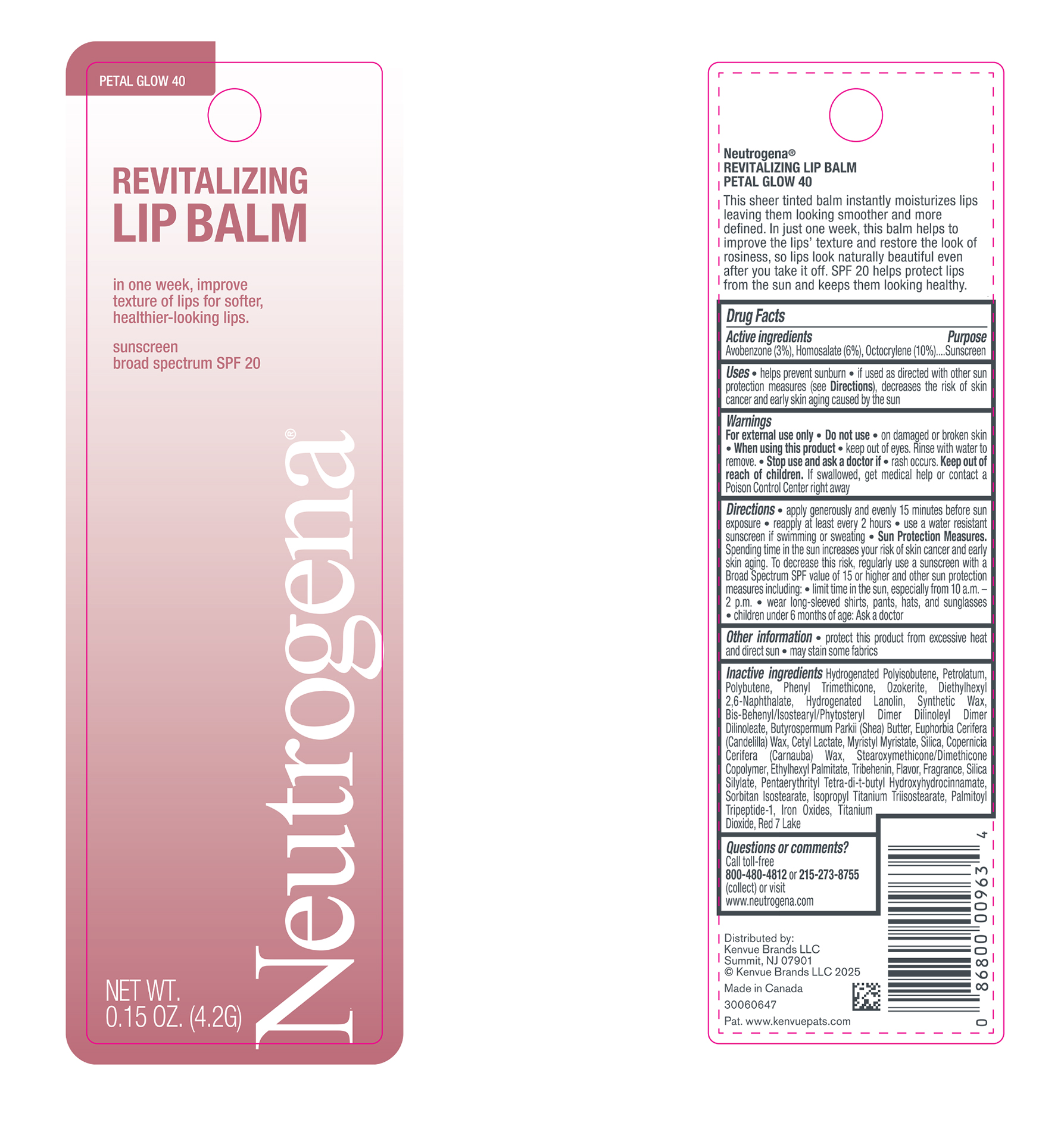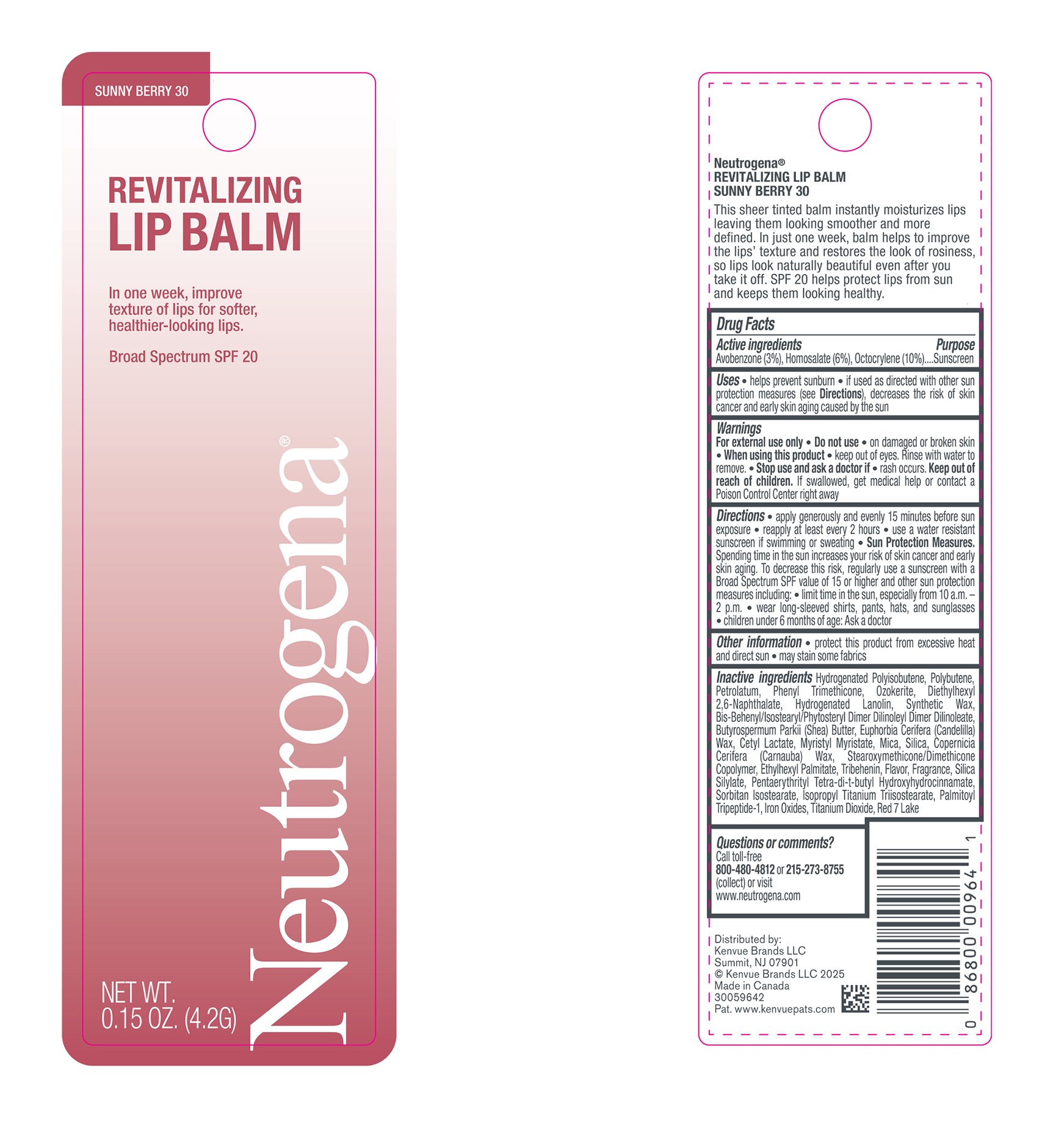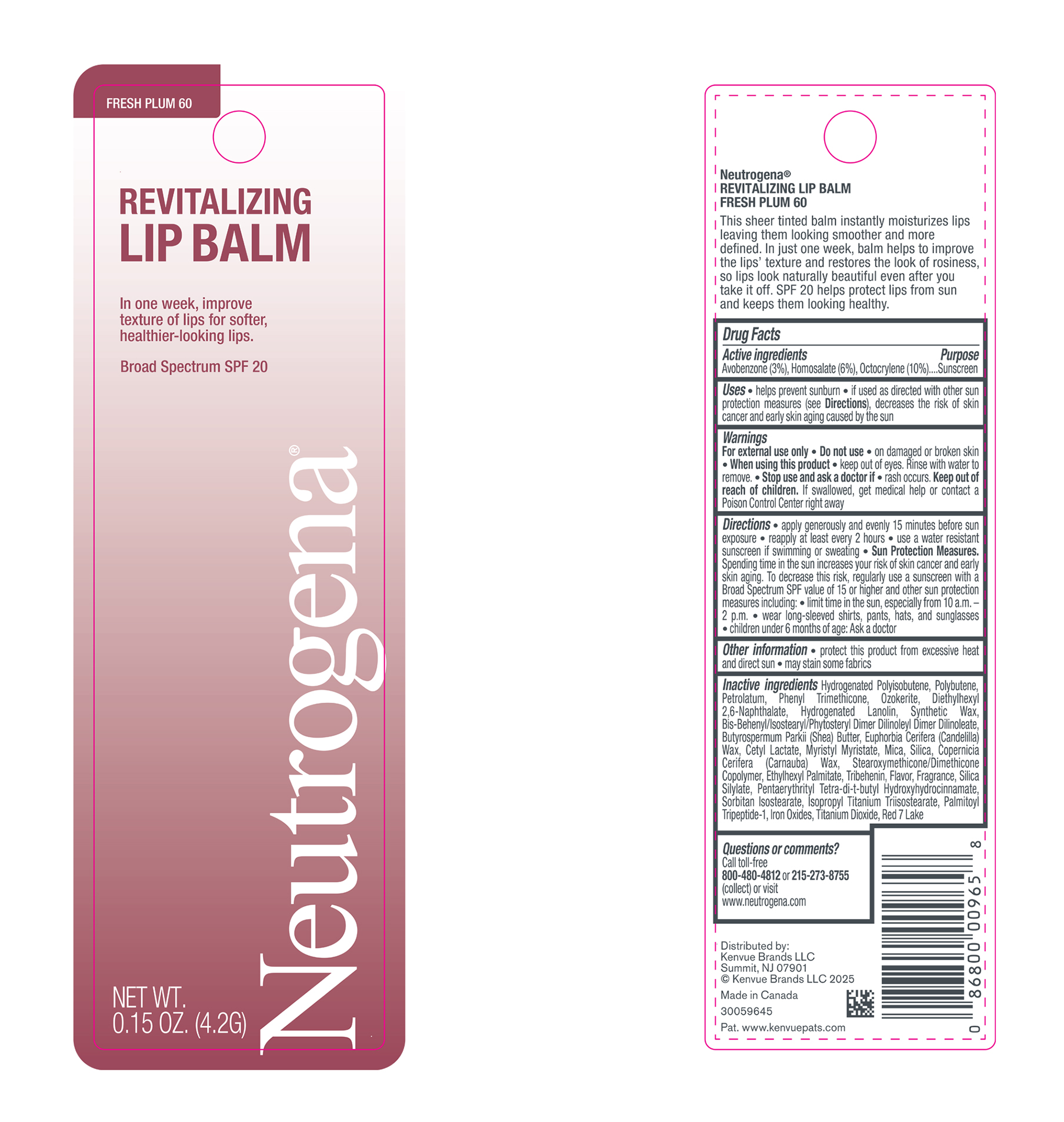 DRUG LABEL: Neutrogena Revitalizing Lip Balm Broad Spectrum SPF 20 - Healthy Blush 20
NDC: 69968-0884 | Form: STICK
Manufacturer: Kenvue Brands LLC
Category: otc | Type: HUMAN OTC DRUG LABEL
Date: 20250908

ACTIVE INGREDIENTS: OCTOCRYLENE 100 mg/1 g; AVOBENZONE 30 mg/1 g; HOMOSALATE 60 mg/1 g
INACTIVE INGREDIENTS: BIS-BEHENYL/ISOSTEARYL/PHYTOSTERYL DIMER DILINOLEYL DIMER DILINOLEATE; POLYBUTENE (1400 MW); PHENYL TRIMETHICONE; LANOLIN ALCOHOLS; CANDELILLA WAX; SORBITAN ISOSTEARATE; TITANIUM DIOXIDE; PETROLATUM; SHEA BUTTER; CERESIN; DIETHYLHEXYL 2,6-NAPHTHALATE; SILICON DIOXIDE; PENTAERYTHRITOL TETRAKIS(3-(3,5-DI-TERT-BUTYL-4-HYDROXYPHENYL)PROPIONATE); FERRIC OXIDE RED; CETYL LACTATE; MYRISTYL MYRISTATE; ETHYLHEXYL PALMITATE; D&C RED NO. 7; CARNAUBA WAX; ISOPROPYL TITANIUM TRIISOSTEARATE; PALMITOYL TRIPEPTIDE-1; TRIBEHENIN; HYDROGENATED POLYISOBUTENE (1300 MW)

Neutrogena Revitalizing Lip Balm Broad Spectrum SPF 20

Drug Facts

Active ingredients

Avobenzone (3%), Homosalate (6%), Octocrylene (10%)

Purpose

Sunscreen

Uses

- helps prevent sunburn
- if used as directed with other sun protection measures (see Directions), decreases the risk of skin cancer and early skin aging caused by the sun

Warnings

- For external use only

■ Do not use

■ on damaged or broken skin

■ When using this product ■ keep out of eyes. Rinse with water to remove.

- Stop use and ask a doctor if ■ rash occurs.

- Keep out of reach of children. If swallowed, get medical help or contact a Poison Control Center right away.

Directions

■ apply generously and evenly 15 minutes before sun exposure ■ reapply at least every 2 hours ■ use a water resistant sunscreen if swimming or sweating ■ Sun Protection Measures. Spending time in the sun increases your risk of skin cancer and early skin aging. To decrease this risk, regularly use a sunscreen with a Broad Spectrum SPF value of 15 or higher and other sun protection measures including: ■ limit time in the sun, especially from 10 a.m. – 2 p.m. ■ wear long-sleeved shirts, pants, hats, and sunglasses

■ children under 6 months of age: Ask a doctor

Other information

- protect this product from excessive heat and direct sun
- may stain some fabrics

Inactive ingredients

Hydrogenated Polyisobutene, Polybutene, Petrolatum, Phenyl Trimethicone, Ozokerite, Diethylhexyl 2,6-Naphthalate, Hydrogenated Lanolin, Synthetic Wax, Bis-Behenyl/Isostearyl/Phytosteryl Dimer Dilinoleyl Dimer Dilinoleate, Butyrospermum Parkii (Shea) Butter, Euphorbia Cerifera (Candelilla) Wax, Cetyl Lactate, Myristyl Myristate, Mica, Silica, Copernicia Cerifera (Carnauba) Wax, Stearoxymethicone/Dimethicone Copolymer, Ethylhexyl Palmitate, Tribehenin, Flavor, Fragrance, Silica Silylate, Pentaerythrityl Tetra-di-t-butyl Hydroxyhydrocinnamate, Sorbitan Isostearate, Isopropyl Titanium Triisostearate, Palmitoyl Tripeptide-1, Iron Oxides,Titanium Dioxide, Red 7 Lake

Questions or comments?

Call toll-free 800-480-4812 or 215-273-8755 (collect) or visit www.neutrogena.com

Distributed by:

Kenvue Brands LLC
Summit, NJ 07901

Drug Facts

Active ingredients

Avobenzone (3%), Homosalate (6%), Octocrylene (10%)

Purpose

Sunscreen

Uses

■ helps prevent sunburn

■ if used as directed with other sun protection measures (see Directions), decreases the risk of skin cancer and early skin aging caused by the sun

Warnings

For external use only

■ Do not use

■ on damaged or broken skin

- When using this product
- keep out of eyes. Rinse with water to remove.

- Stop use and aska doctor if.rash occurs.

- Keep out of reach of children. If swallowed, get medical help or contact a Poison Control Center right away

Directions

■ apply generously and evenly 15 minutes before sun exposure ■ reapply at least every 2 hours ■ use a water resistant sunscreen if swimming or sweating ■ Sun Protection Measures. Spending time in the sun increases your risk of skin cancer and early skin aging. To decrease this risk, regularly use a sunscreen with a Broad Spectrum SPF value of 15 or higher and other sun protection measures including: ■ limit time in the sun, especially from 10 a.m. – 2 p.m. ■ wear long-sleeved shirts, pants, hats, and sunglasses

■ children under 6 months of age: Ask a doctor

Other information

■ protect this product from excessive heat and direct sun

■ may stain some fabrics

Inactive ingredients

Hydrogenated Polyisobutene, Petrolatum, Polybutene, Phenyl Trimethicone, Ozokerite, Diethylhexyl 2,6-Naphthalate, Hydrogenated Lanolin, Synthetic Wax, Bis-Behenyl/Isostearyl/Phytosteryl Dimer Dilinoleyl Dimer Dilinoleate, Butyrospermum Parkii (Shea) Butter, Euphorbia Cerifera (Candelilla) Wax, Cetyl Lactate, Myristyl Myristate, Silica, Copernicia Cerifera (Carnauba) Wax, Stearoxymethicone/Dimethicone Copolymer, Ethylhexyl Palmitate, Tribehenin, Flavor, Fragrance, Silica Silylate, Pentaerythrityl Tetra-di-t-butyl Hydroxyhydrocinnamate, Sorbitan Isostearate, Isopropyl Titanium Triisostearate, Palmitoyl Tripeptide-1, Iron Oxides,Titanium Dioxide, Red 7 Lake

Questions or comments?

Call toll-free

800-480-4812 or 215-273-8755

(collect) or visit

www.neutrogena.com

Distributed by:

Kenvue Brands LLC

Summit, NJ 07901

Drug Facts

Active ingredients

Avobenzone (3%), Homosalate (6%), Octocrylene (10%)

Purpose

Sunscreen

Uses

■ helps prevent sunburn

■ if used as directed with other sun protection measures (see Directions), decreases the risk of skin cancer and early skin aging caused by the sun

Warnings

- For external use only

■ Do not use ■ on damaged or broken skin

■ When using this product

■ keep out of eyes. Rinse with water to remove

- Stop use and ask a doctor if. rash occurs.

- Keep out of reach of children. If swallowed, get medical help or contact a Poison Control Center right away

Directions

■ apply generously and evenly 15 minutes before sun exposure ■ reapply at least every 2 hours ■ use a water resistant sunscreen if swimming or sweating ■ Sun Protection Measures. Spending time in the sun increases your risk of skin cancer and early skin aging. To decrease this risk, regularly use a sunscreen with a Broad Spectrum SPF value of 15 or higher and other

sun protection measures including:■ limit time in the sun, especially from 10 a.m. – 2 p.m.■ wear long-sleeved shirts, pants, hats, and sunglasses■ children under 6 months of age: Ask a doctor

Other information

■ protect this product from excessive heat and direct sun ■ may stain some fabrics

Inactive ingredients

Hydrogenated Polyisobutene, Petrolatum, Polybutene, Phenyl Trimethicone, Ozokerite, Diethylhexyl 2,6-Naphthalate, Hydrogenated Lanolin, Synthetic Wax, Bis-Behenyl/Isostearyl/Phytosteryl Dimer Dilinoleyl Dimer Dilinoleate, Butyrospermum Parkii (Shea) Butter, Euphorbia Cerifera (Candelilla) Wax, Cetyl Lactate, Myristyl Myristate, Silica, Copernicia Cerifera (Carnauba) Wax, Stearoxymethicone/Dimethicone Copolymer, Ethylhexyl Palmitate, Tribehenin, Flavor, Fragrance, Silica Silylate, Pentaerythrityl Tetra-di-t-butyl Hydroxyhydrocinnamate, Sorbitan Isostearate, Isopropyl Titanium Triisostearate, Palmitoyl Tripeptide-1, Mica, Titanium Dioxide, Iron Oxides

Questions or comments?

Call toll-free

800-480-4812 or 215-273-8755

(collect) or visit

www.neutrogena.com

Distributed by:
Kenvue Brands LLC
Summit, NJ 07901

Drug Facts

Active ingredients

Avobenzone (3%), Homosalate (6%), Octocrylene (10%)

Purpose

Sunscreen

Uses

■ helps prevent sunburn

■ if used as directed with other sun protection measures (see Directions), decreases the risk of skin cancer and early skin aging caused by the sun

Warnings

- For external use only

■ Do not use

■ on damaged or broken skin

- When using this product
- keep out of eyes. Rinse with water to remove.

- Stop use and ask a doctor if. rash occurs.

- Keep out of reach of children. If swallowed, get medical help or contact a Poison Control Center right away

Directions

■ apply generously and evenly 15 minutes before sun exposure ■ reapply at least every 2 hours ■ use a water resistant sunscreen if swimming or sweating ■ Sun Protection Measures. Spending time in the sun increases your risk of skin cancer and early skin aging. To decrease this risk, regularly use a sunscreen with a Broad Spectrum SPF value of 15 or higher and other

sun protection measures including:■ limit time in the sun, especially from 10 a.m. – 2 p.m. ■ wear long-sleeved shirts, pants, hats, and sunglasses ■ children under 6 months of age: Ask a doctor

Other information

■ protect this product from excessive heat and direct sun

■ may stain some fabrics

Inactive ingredients

Hydrogenated Polyisobutene, Petrolatum, Polybutene, Phenyl Trimethicone, Ozokerite, Diethylhexyl 2,6-Naphthalate, Hydrogenated Lanolin, Synthetic Wax, Bis-Behenyl/Isostearyl/Phytosteryl Dimer Dilinoleyl Dimer Dilinoleate, Butyrospermum Parkii (Shea) Butter, Euphorbia Cerifera (Candelilla) Wax, Cetyl Lactate, Myristyl Myristate, Silica, Copernicia Cerifera (Carnauba) Wax, Stearoxymethicone/Dimethicone Copolymer, Ethylhexyl Palmitate, Tribehenin, Flavor, Fragrance, Silica Silylate, Pentaerythrityl Tetra-di-t-butyl Hydroxyhydrocinnamate, Sorbitan Isostearate, Isopropyl Titanium Triisostearate, Palmitoyl Tripeptide-1,Titanium Dioxide, Red 6 Lake, Red 7 Lake, Iron Oxides

Questions or comments?

Call toll-free

800-480-4812 or 215-273-8755

(collect) or visit

www.neutrogena.com

Distributed by:
Kenvue Brands LLC
Summit, NJ 07901

Neutrogena Revitalizing Lip Balm Broad Spectrum SPF 20 - 4.2g Canister in Blister Pack Label - Sunny Berry 30

SUNNY BERRY 30

REVITALIZING

LIP BALM

In one week, improve

texture of lips for softer,

healthier-looking lips.

Broad Spectrum SPF 20

Neutrogena®

NET WT.

0.15 OZ. (4.2G)

Neutrogena Revitalizing Lip Balm Broad Spectrum SPF 20 - 4.2g Canister in Blister Pack Label - Sheer Shimmer 10

SHEER SHIMMER 10

REVITALIZING

LIP BALM

In one week, improve

texture of lips for softer,

healthier-looking lips.

sunscreen

Broad Spectrum SPF 20

Neutrogena®

NET WT.

0.15 OZ. (4.2G)

Neutrogena Revitalizing Lip Balm Broad Spectrum SPF 20 - 4.2g Canister in Blister Pack Label - Fresh Plum 60

FRESH PLUM 60

REVITALIZING

LIP BALM

In one week, improve

texture of lips for softer,

healthier-looking lips.

Broad Spectrum SPF 20

Neutrogena®

NET WT.

0.15 OZ. (4.2G)

Neutrogena Revitalizing Lip Balm Broad Spectrum SPF 20 - 4.2g Canister in Blister Pack Label - Petal Glow 40

PETAL GLOW 40

REVITALIZING

LIP BALM

in one week, improve

texture of lips for softer,

healthier-looking lips.

sunscreen

broad spectrum SPF 20

Neutrogena®

NET WT.

0.15 OZ. (4.2G)

Neutrogena Revitalizing Lip Balm Broad Spectrum SPF 20 - 4.2g Canister in Blister pack Label - Soft Caramel 50

SOFT CARAMEL 50

REVITALIZING

LIP BALM

In one week, improve

texture of lips for softer,

healthier-looking lips.

sunscreen

Broad Spectrum SPF 20

Neutrogena®

NET WT.

0.15 OZ. (4.2G)

Neutrogena Revitalizing Lip Balm Broad Spectrum SPF 20 - 4.2g Canister in Blister pack Label - Healthy Blush 20

HEALTHY BLUSH 20

REVITALIZING

LIP BALM

in one week, improve

texture of lips for softer,

healthier-looking lips.

sunscreen

broad spectrum SPF 20

Neutrogena®

NET WT.

0.15 OZ. (4.2G)